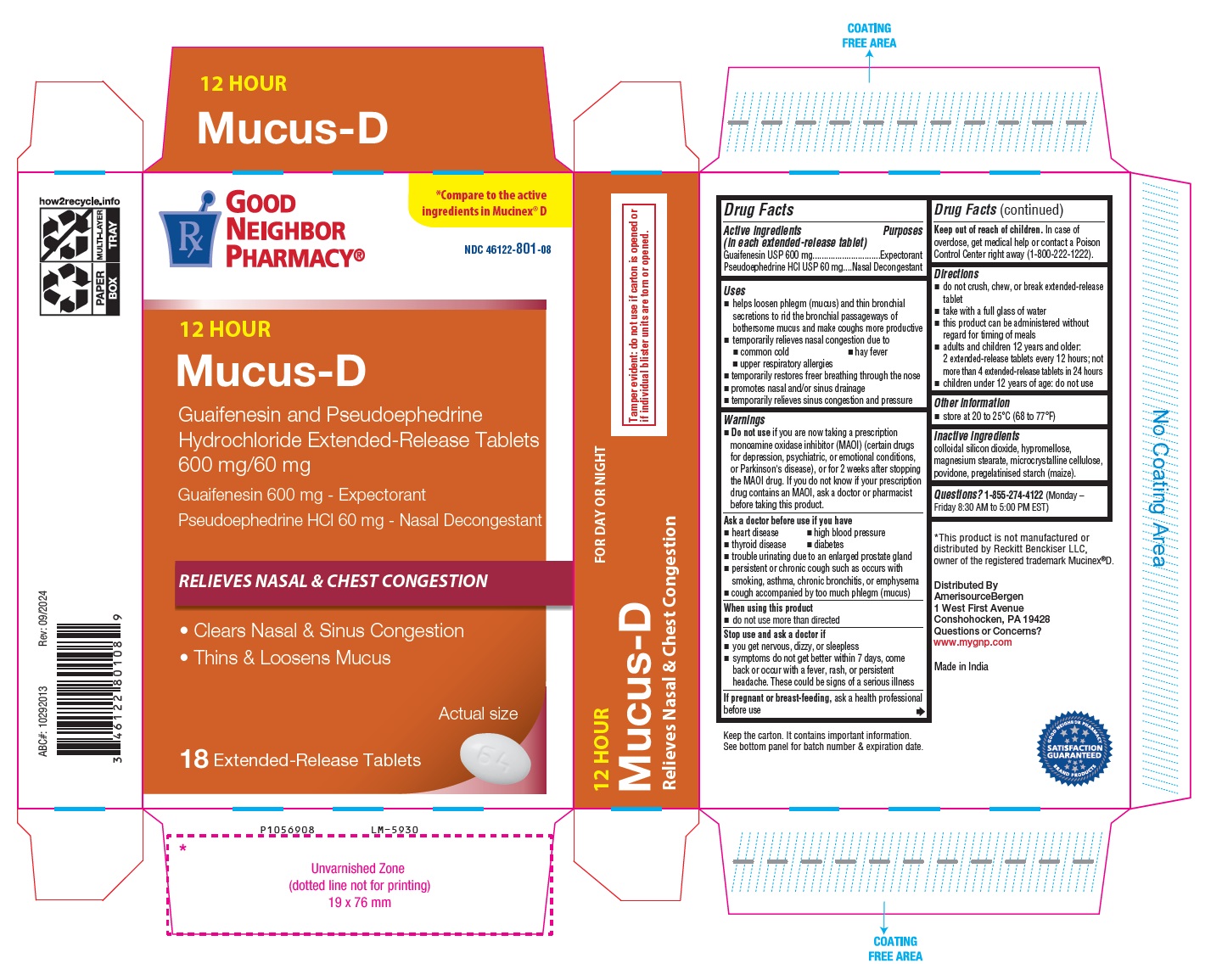 DRUG LABEL: Guaifenesin and Pseudoephedrine HCl
NDC: 46122-801 | Form: TABLET, EXTENDED RELEASE
Manufacturer: Amerisource Bergen
Category: otc | Type: Human OTC Drug Label
Date: 20241203

ACTIVE INGREDIENTS: GUAIFENESIN 600 mg/1 1; PSEUDOEPHEDRINE HYDROCHLORIDE 60 mg/1 1
INACTIVE INGREDIENTS: SILICON DIOXIDE; HYPROMELLOSE 2208 (15000 MPA.S); MAGNESIUM STEARATE; MICROCRYSTALLINE CELLULOSE 101; MICROCRYSTALLINE CELLULOSE 102; POVIDONE K25; POVIDONE K90; STARCH, CORN

Drug Facts

Active ingredients

(in each extended-release tablet)
Guaifenesin USP 600 mg

Pseudoephedrine HCl USP 60 mg

Purposes

Expectorant

Nasal Decongestant

Uses

- helps loosen phlegm (mucus) and thin bronchial secretions to rid the bronchial passageways of bothersome mucus and make coughs more productive
- temporarily relieves nasal congestion due to
  - common cold
  - hay fever
  - upper respiratory allergies
- temporarily restores freer breathing through the nose
- promotes nasal and/or sinus drainage
- temporarily relieves sinus congestion and pressure

Warnings

- Do not use if you are now taking a prescription monoamine oxidase inhibitor (MAOI) (certain drugs for depression, psychiatric, or emotional conditions, or Parkinson's disease), or for 2 weeks after stopping the MAOI drug. If you do not know if your prescription drug contains an MAOI, ask a doctor or pharmacist before taking this product.

Ask a doctor before use if you have

- heart disease
- high blood pressure
- thyroid disease
- diabetes
- trouble urinating due to an enlarged prostate gland
- persistent or chronic cough such as occurs with smoking, asthma, chronic bronchitis, or emphysema
- cough accompanied by too much phlegm (mucus)

When using this product

- do not use more than directed

Stop use and ask a doctor if

- you get nervous, dizzy, or sleepless
- symptoms do not get better within 7 days, come back or occur with a fever, rash, or persistent headache. These could be signs of a serious illness

If pregnant or breast-feeding,

ask a health professional before use

Keep out of reach of children.

In case of overdose, get medical help or contact a Poison Control Center right away (1-800-222-1222).

Directions

- do not crush, chew, or break extended-release tablet
- take with a full glass of water
- this product can be administered without regard for timing of meals
- adults and children 12 years and older: 2 extended-release tablets every 12 hours; not more than 4 extended-release tablets in 24 hours
- children under 12 years of age: do not use

Other information

- store at 20 to 25°C (68 to 77°F)

Inactive ingredients

colloidal silicon dioxide, hypromellose, magnesium stearate, microcrystalline cellulose, povidone, pregelatinised starch (maize).

Questions?

1-855-274-4122 (Monday – Friday 8:30 AM to 5:00 PM EST)
Distributed By
AmerisourceBergen
1 West First Avenue
Conshohocken, PA 19428
Questions or Concerns?
www.mygnp.com
Made in India

PACKAGE LABEL-PRINCIPAL DISPLAY PANEL - 600 mg/60 mg (18 Tablet Carton Label)

℞ GOOD *Compare to the
NEIGHBOR active ingredients in Mucinex® D
PHARMACY®
NDC 46122-801-08
12 HOUR
Mucus-D
Guaifenesin and Pseudoephedrine
Hydrochloride Extended-Release Tablets
600 mg/60 mg
Guaifenesin 600 mg - Expectorant
Pseudoephedrine HCl 60 mg - Nasal Decongestant
RELIEVES NASAL & CHEST CONGESTION
• Clears Nasal & Sinus Congestion
• Thins & Loosens Mucus
Actual size
18 Extended-Release Tablets